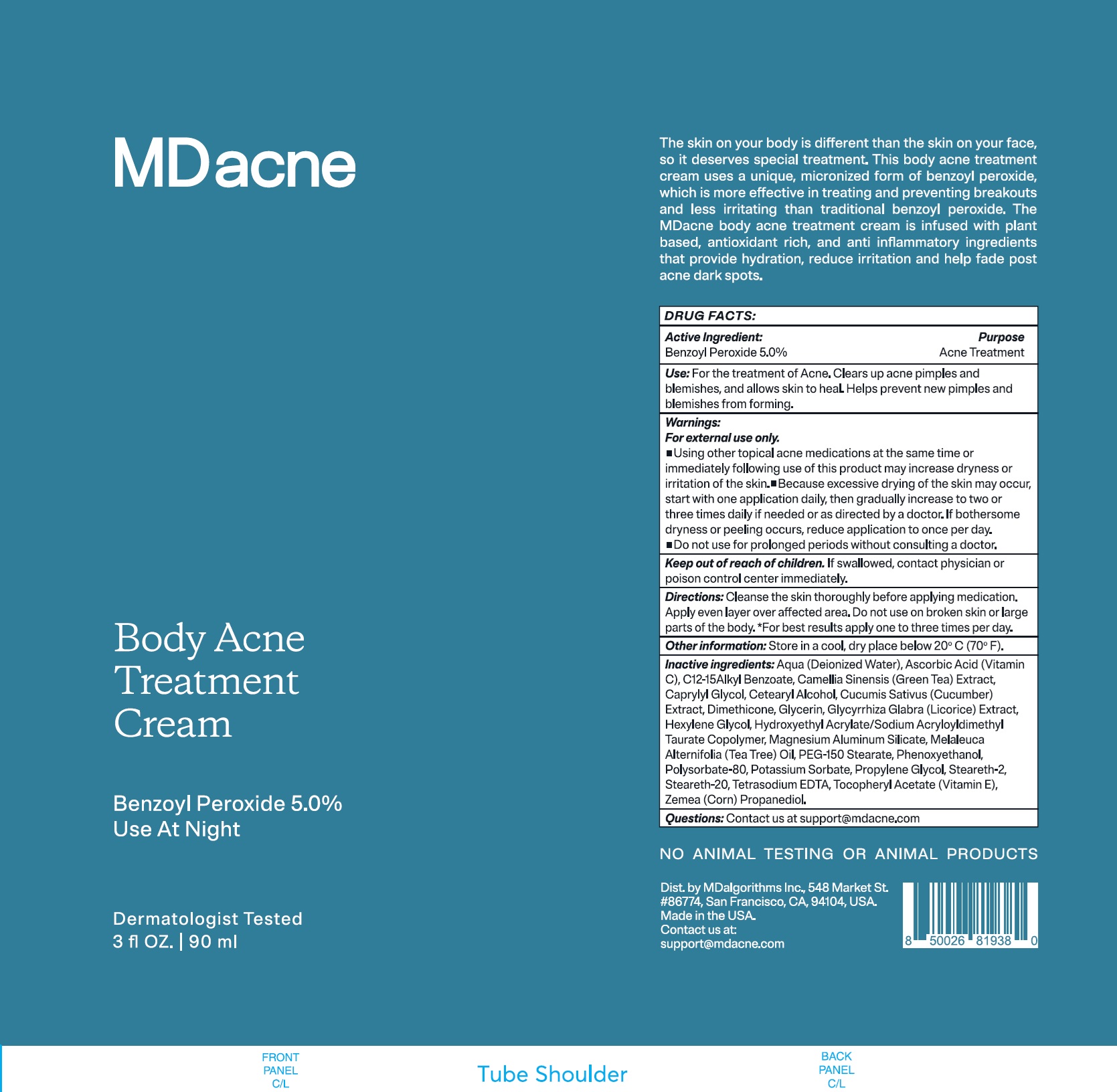 DRUG LABEL: MDacne Body Acne Treatment Benzoyl Peroxide
NDC: 71804-532 | Form: CREAM
Manufacturer: MDAlgorithms Inc
Category: otc | Type: HUMAN OTC DRUG LABEL
Date: 20240919

ACTIVE INGREDIENTS: BENZOYL PEROXIDE 50 mg/1 mL
INACTIVE INGREDIENTS: WATER; ASCORBIC ACID; ALKYL (C12-15) BENZOATE; GREEN TEA LEAF; CAPRYLYL GLYCOL; CETOSTEARYL ALCOHOL; CUCUMBER; DIMETHICONE, UNSPECIFIED; GLYCERIN; GLYCYRRHIZA GLABRA; HEXYLENE GLYCOL; MAGNESIUM ALUMINUM SILICATE; MELALEUCA ALTERNIFOLIA LEAF; PEG-150 STEARATE; PHENOXYETHANOL; POLYSORBATE 80; POTASSIUM SORBATE; PROPYLENE GLYCOL; STEARETH-2; STEARETH-20; EDETATE SODIUM; .ALPHA.-TOCOPHEROL ACETATE; CORN

MDacne Body Acne Treatment Cream Benzoyl Peroxide 5%

Active Ingredient:

Benzoyl Peroxide 5.0%

Purpose

Acne Treatment

Use:

For the treatment of Acne. Clears up acne pimples and blemishes, and allows skin to heal. Helps prevent new pimples and blemishes from forming.

Warnings:

For external use only.

- Using other topical acne medications at the same time or immediately following use of this product may increase dryness or irritation of the skin.
  Because excessive drying of the skin may occur, start with one application daily, then gradually increase to two or three times daily if needed or as directed by a doctor. If bothersome dryness or peeling occurs, reduce application to once per day.

• Do not use

for prolonged periods without consulting a doctor.

Keep out of reach of children.

If swallowed, contact physician or Poison Control Center immediately.

Directions:

Cleanse the skin thoroughly before applying medication. Apply even layer over affected area. Do not use on broken skin or large parts of the body. *For best results apply one to three times per day.

Other information:

Store in a cool, dry place below 20ºC (70ºF).

Inactive Ingredients:

Aqua (Deionized Water), Ascorbic Acid (Vitamin C), C12-15 Alkyl Benzoate, Camellia Sinensis (Green Tea) Extract, Caprylyl Glycol, Cetearyl Alcohol, Cucumis Sativus (Cucumber) Extract, Dimethicone, Glycerin, Glycyrrhiza Glabra (Licorice) Extract, Hexylene Glycol, Hydroxyethyl Acrylate/Sodium Acryloyldimethyl Taurate Copolymer, Magnesium Aluminum Silicate, Melaleuca Alternifolia (Tea Tree) Oil, PEG-150 Stearate, Phenoxyethanol, Polysorbate-80, Potassium Sorbate, Propylene Glycol, Steareth-2, Steareth-20, Tetrasodium EDTA, Tocopheryl Acetate (Vitamin E), Zemea (Corn) Propanediol.

Questions:

Contact us at support@mdacne.com